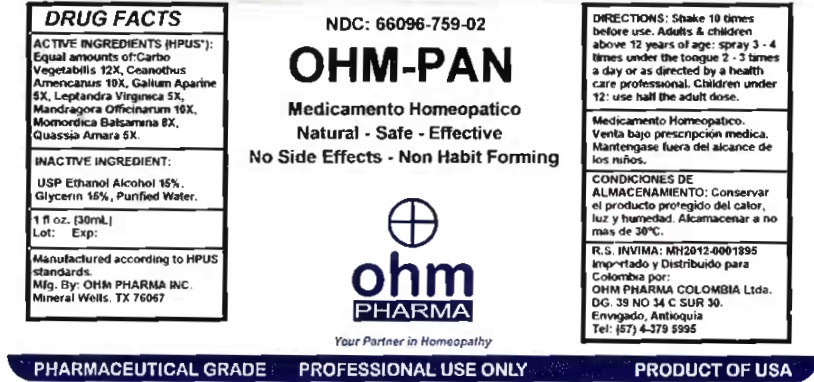 DRUG LABEL: OHM-PAN
NDC: 66096-759 | Form: SPRAY
Manufacturer: OHM PHARMA INC.
Category: homeopathic | Type: HUMAN PRESCRIPTION DRUG LABEL
Date: 20260128

ACTIVE INGREDIENTS: ACTIVATED CHARCOAL 12 [hp_X]/30 mL; CEANOTHUS AMERICANUS LEAF 10 [hp_X]/30 mL; GALIUM APARINE 5 [hp_X]/30 mL; VERONICASTRUM VIRGINICUM ROOT 5 [hp_X]/30 mL; MANDRAGORA OFFICINARUM ROOT 10 [hp_X]/30 mL; MOMORDICA BALSAMINA IMMATURE FRUIT 8 [hp_X]/30 mL; QUASSIA AMARA WOOD 5 [hp_X]/30 mL
INACTIVE INGREDIENTS: ALCOHOL; GLYCERIN; WATER

OHM-PAN

ACTIVE INGREDIENT

ACTIVE INGREDIENTS (HPUS*): Equal amounts of: Carbo Vegetabilis 12X, Ceanothus Americanus 10X, Galium Aparine 5X, Leptandra Virginica 5X, Mandragora Officinarum 10X, Momordica Balsamina 8X, Quassia Amara 5X.

INDICATIONS AND USAGE

USES: Temporarily relieves functional ailments of the endocrine/exocrine pancreas.**

WARNINGS

Medicamento Homeopatico. Venta bajo prescripcion medica. Mantengase fuera del alcance de los niños.

KEEP OUT OF REACH OF CHILDREN

Medicamento Homeopatico. Venta bajo prescripcion medica. Mantengase fuera del alcance de los niños.

DOSAGE AND ADMINISTRATION

Shake 10 times before use. Adults & children above 12 years of age: spray 3 - 4 times under the tongue 2 - 3 times a day or as directed by a health care professional. Children under 12: use half the adult dose.

OTHER SAFETY INFORMATION

CONDICIONES DE ALMACENAMIENTO: Conservar el producto protegido del calor, luz y humedad. Alcamacenar a no mas de 30°C.

INACTIVE INGREDIENT:

USP Ethanol Alcohol 15%, Glycerin 15% Purified Water.

QUESTIONS

I mportado y distribuido para Colombia por
OHM PHARMA COLOMBIA SAS
Vereda El Abra
Sector Saunas Medicas
Finca el Rinconcito
Cota, Cundinamarca, Colombia
Tel: (+57) 320-230-7789

R.S. INVIMA: MH2012-0001895

Manufactured according to HPUS

standards.

Mfg. By: OHM PHARMA INC.

Mineral Wells, TX 76067

PACKAGE LABEL

NDC: 66096-759-02

OHM-PAN

Medicamento Homeopatico

Natural - Safe - Effective

No Side Effects - Non Habit Forming

PURPOSE

USES: Temporarily relieves functional ailments of the endocrine/exocrine pancreas.**